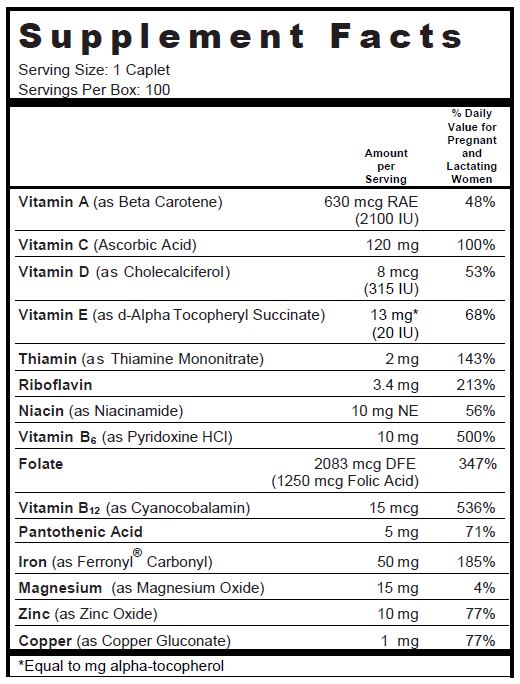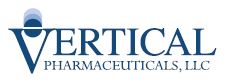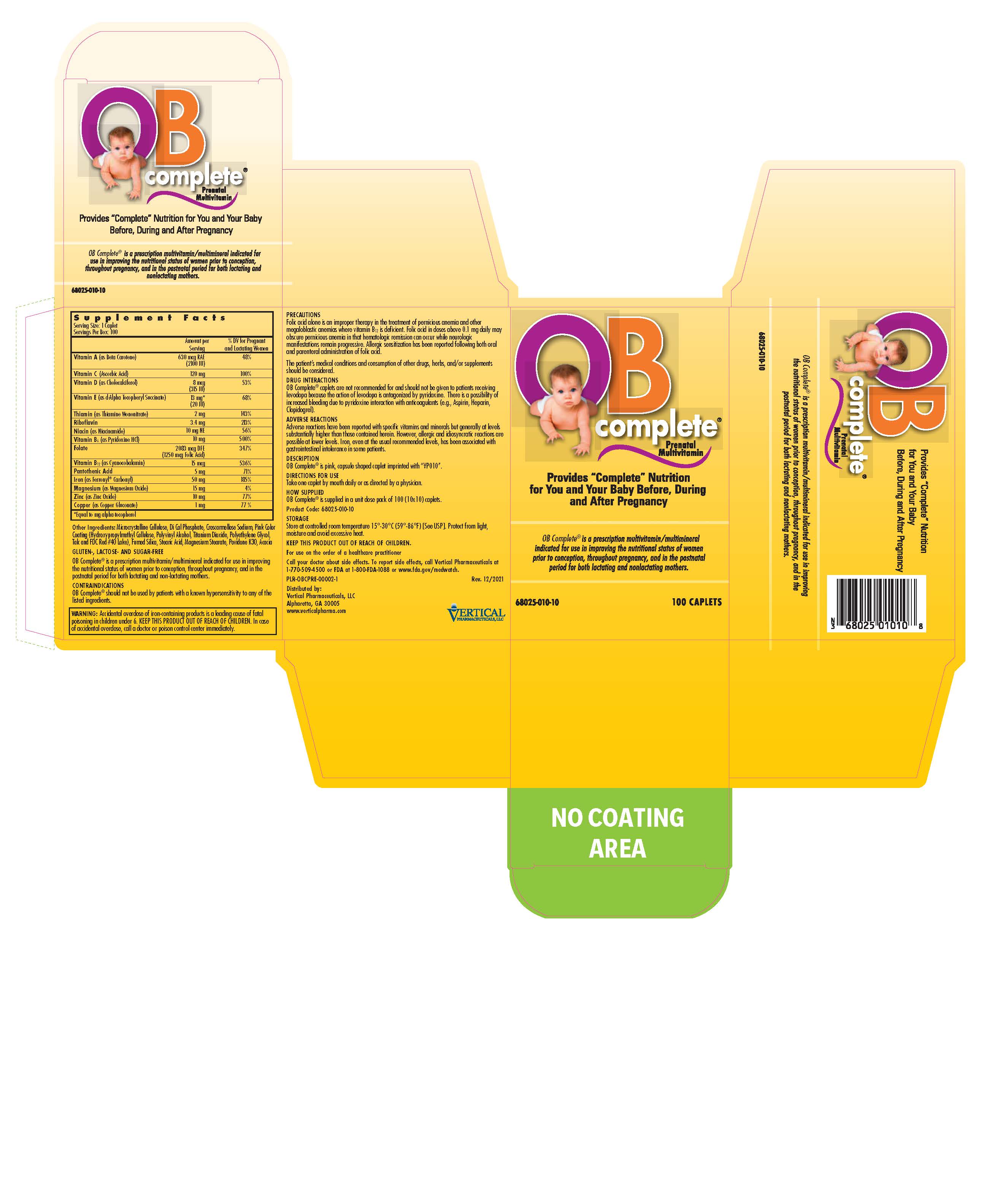 DRUG LABEL: OB Complete Prenatal
NDC: 68025-010 | Form: TABLET
Manufacturer: Vertical Pharmaceuticals, LLC
Category: other | Type: DIETARY SUPPLEMENT
Date: 20191211

ACTIVE INGREDIENTS: BETA CAROTENE 2100 [iU]/1 1; ascorbic acid 120 mg/1 1; cholecalciferol 315 [iU]/1 1; .alpha.-tocopherol succinate, D- 20 [iU]/1 1; THIAMINE MONONITRATE 2 mg/1 1; Riboflavin 3.4 mg/1 1; NIACINAMIDE 10 mg/1 1; Pyridoxine Hydrochloride 10 mg/1 1; Folic Acid 1.25 mg/1 1; Cyanocobalamin 15 ug/1 1; Pantothenic Acid 5 mg/1 1; IRON PENTACARBONYL 50 mg/1 1; Magnesium Oxide 15 mg/1 1; Zinc Oxide 10 mg/1 1; COPPER GLUCONATE 1 mg/1 1
INACTIVE INGREDIENTS: cellulose, microcrystalline; CALCIUM PHOSPHATE, DIBASIC, ANHYDROUS; Croscarmellose Sodium; hypromelloses; POLYVINYL ALCOHOL, UNSPECIFIED; titanium dioxide; POLYETHYLENE GLYCOL, UNSPECIFIED; Talc; FD&C Red No. 40; SILICON DIOXIDE; stearic acid; Magnesium Stearate; povidone K30; acacia

OB COMPLETE® PRENATAL MULTIVITAMIN

SUPPLEMENT FACTS

Other Ingredients: Microcrystalline Cellulose, Di Cal Phosphate, Croscarmellose Sodium, Pink Color Coating (Hydroxypropylmethyl Cellulose, Polyvinyl Alcohol, Titanium Dioxide, Polyethylene Glycol, Talc and FDC Red #40 Lake), Fumed Silica, Stearic Acid, Magnesium Stearate, Povidone K30, Acacia

GLUTEN-, LACTOSE- AND SUGAR-FREE

OB Complete® is a prescription multivitamin/multimineral indicated for use in improving the nutritional status of women prior to conception, throughout pregnancy, and in the postnatal period for both lactating and non-lactating mothers.

HEALTH CLAIM

Other Ingredients: Microcrystalline Cellulose, Di Cal Phosphate, Croscarmellose Sodium, Pink Color Coating (Hydroxypropylmethyl Cellulose, Polyvinyl Alcohol, Titanium Dioxide, Polyethylene Glycol, Talc, FD&C Red #40 Lake), Fumed Silica, Stearic Acid, Magnesium Stearate, Povidone K30, Acacia.

GLUTEN, SUGAR AND LACTOSE FREE

CONTRAINDICATIONS

OB Complete® should not be used by patients with a known hypersensitivity to any of the listed ingredients.

WARNINGS

WARNING: Accidental overdose of iron-containing products is a leading cause of fatal poisoning in children under 6. KEEP THIS PRODUCT OUT OF REACH OF CHILDREN. In case of accidental overdose, call a doctor or poison control center immediately.

PRECAUTIONS

Folic acid alone is an improper therapy in the treatment of pernicious anemia and other megaloblastic anemias where vitamin B12 is deficient. Folic acid in doses above 0.1 mg daily may obscure pernicious anemia in that hematologic remission can occur while neurologic manifestations remain progressive. Allergic sensitization has been reported following both oral and parenteral administration of folic acid.

The patient’s medical conditions and consumption of other drugs, herbs, and/or supplements should be considered.

DRUG INTERACTIONS

OB Complete® caplets are not recommended for and should not be given to patients receiving levodopa because the action of levodopa is antagonized by pyridoxine. There is a possibility of increased bleeding due to pyridoxine interaction with anticoagulants (e.g., Aspirin, Heparin, Clopidogrel).

ADVERSE REACTIONS

Adverse reactions have been reported with specific vitamins and minerals but generally at levels substantially higher than those contained herein. However, allergic and idiosyncratic reactions are possible at lower levels. Iron, even at the usual recommended levels, has been associated with gastrointestinal intolerance in some patients

DESCRIPTION

OB Complete® is pink, capsule shaped caplet imprinted with "VP010".

DIRECTIONS FOR USE

Take one caplet by mouth daily or as directed by a physician.

HOW SUPPLIED

OB Complete® is supplied in a unit dose pack of 100 (10x10) caplets.

Product Code: 68025-010-10

STORAGE

Store at controlled room temperature 15°-30°C (59°-86°F) [See USP]. Protect from light, moisture and avoid excessive heat.

WARNINGS

KEEP THIS PRODUCT OUT OF REACH OF CHILDREN.

For use on the order of a healthcare practitioner

Call your doctor about side effects. To report side effects, call Vertical Pharmaceuticals at 1-770-509-4500 or FDA at 1-800-FDA-1088 or www.fda.gov/medwatch.

PLR-OBCPRE-00002-1 Rev. 12/2021

Distributed by:

Vertical Pharmaceuticals, LLC

Alpharetta, GA 30005

www.verticalpharma.com

PRINCIPAL DISPLAY PANEL - 100 Caplet Blister Pack Carton

OB Complete® Prenatal Multivitamin

NDC 68025-010-10
100 CAPLETS